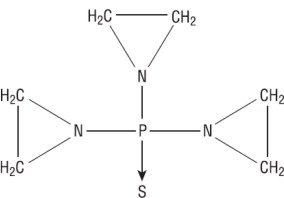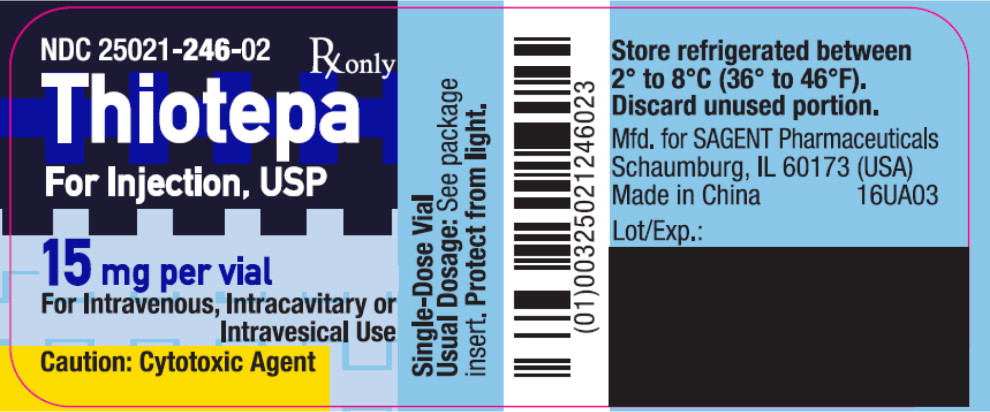 DRUG LABEL: Thiotepa
NDC: 25021-246 | Form: INJECTION, POWDER, LYOPHILIZED, FOR SOLUTION
Manufacturer: Sagent Pharmaceuticals
Category: prescription | Type: HUMAN PRESCRIPTION DRUG LABEL
Date: 20251020

ACTIVE INGREDIENTS: Thiotepa 15 mg/1.5 mL

THIOTEPA FOR INJECTION, USP
(For Intravenous, Intracavitary or Intravesical Use)

sagent®
Rx only

DESCRIPTION

Thiotepa for Injection, USP is an ethylenimine-type compound. It is supplied as a non-pyrogenic, sterile lyophilized powder for intravenous, intracavitary or intravesical administration, containing 15 mg of thiotepa. Thiotepa is a synthetic product with antitumor activity. The chemical name for thiotepa is Aziridine, 1,1',1''-phosphinothioylidynetris-, or Tris (1-aziridinyl) phosphine sulfide. Thiotepa has the following structural formula:

Thiotepa has the empirical formula C6H12N3PS, and a molecular weight of 189.22. When reconstituted with sterile water for injection, the resulting solution has a pH of approximately 5.5 to 7.5. Thiotepa is stable in alkaline medium and unstable in acid medium.

CLINICAL PHARMACOLOGY

Thiotepa is a cytotoxic agent of the polyfunctional type, related chemically and pharmacologically to nitrogen mustard. The radiomimetic action of thiotepa is believed to occur through the release of ethylenimine radicals which, like irradiation, disrupt the bonds of DNA. One of the principal bond disruptions is initiated by alkylation of guanine at the N-7 position, which severs the linkage between the purine base and the sugar and liberates alkylated guanines.

The pharmacokinetics of thiotepa and TEPA in thirteen female patients (45 to 84 years) with advanced stage ovarian cancer receiving 60 mg and 80 mg thiotepa by intravenous infusion on subsequent courses given at 4 week intervals are presented in the following table:

Pharmacokinetic Parameters (units) | Mean ± SEM
Pharmacokinetic Parameters (units) | Thiotepa |  | TEPA
Pharmacokinetic Parameters (units) | 60 mg | 80 mg | 60 mg | 80 mg
Peak Serum concentration (ng/mL) | 1331 ± 119 | 1828 ± 135 | 273 ± 46 | 353 ± 46
Elimination half-life (h) | 2.4 ± 0.3 | 2.3 ± 0.3 | 17.6 ± 3.6 | 15.7 ± 2.7
Area under the curve (ng/h/mL) | 2832 ± 412 | 4127 ± 668 | 4789 ± 1022 | 7452 ± 1667
Total body clearance (mL/min) | 446 ± 63 | 419 ± 56

TEPA, which possesses cytotoxic activity, appears to be the major metabolite of thiotepa found in human serum and urine. Urinary excretion of ^14C-labeled thiotepa and metabolites in a 34 year old patient with metastatic carcinoma of the cecum who received a dose of 0.3 mg/kg intravenously was 63%. Thiotepa and TEPA in urine each accounts for less than 2% of the administered dose.

The pharmacokinetics of thiotepa in renal and hepatic dysfunction patients have not been evaluated. Possible pharmacokinetic interactions of thiotepa with any concomitantly administered medications have not been formally investigated.

INDICATIONS AND USAGE

Thiotepa for Injection has been tried with varying results in the palliation of a wide variety of neoplastic diseases. However, the most consistent results have been seen in the following tumors:

1. Adenocarcinoma of the breast.
2. Adenocarcinoma of the ovary.
3. For controlling intracavitary effusions secondary to diffuse or localized neoplastic diseases of various serosal cavities.
4. For the treatment of superficial papillary carcinoma of the urinary bladder.

While now largely superseded by other treatments, Thiotepa for Injection has been effective against other lymphomas, such as lymphosarcoma and Hodgkin's disease.

CONTRAINDICATIONS

Thiotepa is contraindicated in patients with a known hypersensitivity (allergy) to this preparation.

Therapy is probably contraindicated in cases of existing hepatic, renal, or bone-marrow damage. However, if the need outweighs the risk in such patients, thiotepa may be used in low dosage, and accompanied by hepatic, renal and hemopoietic function tests.

WARNINGS

Death has occurred after intravesical administration, caused by bone-marrow depression from systematically absorbed drug.

Death from septicemia and hemorrhage has occurred as a direct result of hematopoietic depression by thiotepa.

Thiotepa is highly toxic to the hematopoietic system. A rapidly falling white blood cell or platelet count indicates the necessity for discontinuing or reducing the dosage of thiotepa. Weekly blood and platelet counts are recommended during therapy and for at least 3 weeks after therapy has been discontinued.

Thiotepa can cause fetal harm when administered to a pregnant woman. Thiotepa given by the intraperitoneal (IP) route was teratogenic in mice at doses ≥1 mg/kg (3.2 mg/m^2), approximately 8-fold less than the maximum recommended human therapeutic dose (0.8 mg/kg, 27 mg/m^2), based on body-surface area. Thiotepa given by the IP route was teratogenic in rats at doses ≥3 mg/kg (21 mg/m^2), approximately equal to the maximum recommended human therapeutic dose, based on body-surface area. Thiotepa was lethal to rabbit fetuses at a dose of 3 mg/kg (41 mg/m^2), approximately two times the maximum recommended human therapeutic dose based on body-surface area.

Effective contraception should be used during thiotepa therapy if either the patient or partner is of childbearing potential. There are no adequate and well-controlled studies in pregnant women. If thiotepa is used during pregnancy, or if pregnancy occurs during thiotepa therapy, the patient and partner should be apprised of the potential hazard to the fetus.

Thiotepa is a polyfunctional alkylating agent, capable of cross-linking the DNA within a cell and changing its nature. The replication of the cell is, therefore, altered, and thiotepa may be described as mutagenic. An in vitro study has shown that it causes chromosomal aberrations of the chromatid type and that the frequency of induced aberrations increases with the age of the subject.

Like many alkylating agents, thiotepa has been reported to be carcinogenic when administered to laboratory animals. Carcinogenicity is shown most clearly in studies using mice, but there is some evidence of carcinogenicity in man. In patients treated with thiotepa, cases of myelodysplastic syndromes and acute non-lymphocytic leukemia have been reported.

PRECAUTIONS

General

The serious complication of excessive thiotepa therapy, or sensitivity to the effects of thiotepa, is bone-marrow depression. If proper precautions are not observed thiotepa may cause leukopenia, thrombocytopenia, and anemia.

Information for Patients

The patient should notify the physician in the case of any sign of bleeding (epistaxis, easy bruising, change in color of urine, black stool) or infection (fever, chills) or for possible pregnancy to patient or partner.

Effective contraception should be used during thiotepa therapy if either the patient or the partner is of childbearing potential.

Laboratory Tests

The most reliable guide to thiotepa toxicity is the white blood cell count. If this falls to 3,000 or less, the dose should be discontinued. Another good index of thiotepa toxicity is the platelet count; if this falls to 150,000, therapy should be discontinued. Red blood cell count is a less accurate indicator of thiotepa toxicity. If the drug is used in patients with hepatic or renal damage (see CONTRAINDICATIONS section), regular assessment of hepatic and renal function tests are indicated.

Drug Interactions

It is not advisable to combine, simultaneously or sequentially, cancer chemotherapeutic agents or a cancer chemotherapeutic agent and a therapeutic modality having the same mechanism of action. Therefore, thiotepa combined with other alkylating agents such as nitrogen mustard or cyclophosphamide or thiotepa combined with irradiation would serve to intensify toxicity rather than to enhance therapeutic response. If these agents must follow each other, it is important that recovery from the first agent, as indicated by white blood cell count, be complete before therapy with the second agent is instituted.

Other drugs which are known to produce bone-marrow depression should be avoided.

Carcinogenesis, Mutagenesis, Impairment of Fertility

Also see WARNINGS section.

Carcinogenesis

In mice, repeated IP administration of thiotepa (1.15 or 2.3 mg/kg three times per week for 52 or 43 weeks, respectively) produced a significant increase in the combined incidence of squamous-cell carcinomas of the skin, preputial gland, and ear canal, and combined incidence of lymphoma and lymphocytic leukemia. In other studies in mice, repeated IP administration of thiotepa (4 or 8 mg/kg three times per week for 4 weeks followed by a 20 week observation period or 1.8 mg/kg three times per week for 4 weeks followed by a 35 week observation period) resulted in an increased incidence of lung tumors. In rats, repeated IP administration of thiotepa (0.7 or 1.4 mg/kg three times per week for 52 or 34 weeks, respectively) produced significant increases in the incidence of squamous-cell carcinomas of the skin or ear canal, combined hematopoietic neoplasms, and uterine adenocarcinomas. Thiotepa given intravenously (IV) to rats (1 mg/kg once per week for 52 weeks) produced an increased incidence of malignant tumors (abdominal cavity sarcoma, lymphosarcoma myelosis, seminoma, fibrosarcoma, salivary gland hemangioendothelioma, mammary sarcoma, pheochromocytoma) and benign tumors.

The lowest reported carcinogenic dose in mice (1.15 mg/kg, 3.68 mg/m^2) is approximately 7-fold less than the maximum recommended human therapeutic dose based on body-surface area. The lowest reported carcinogenic dose in rats (0.7 mg/kg, 4.9 mg/m^2) is approximately 6-fold less than the maximum recommended human therapeutic dose based on body-surface area.

Mutagenesis

Thiotepa was mutagenic in in vitro assays in Salmonella typhimurium, E coli, Chinese hamster lung and human lymphocytes. Chromosomal aberrations and sister chromatid exchanges were observed in vitro with thiotepa in bean root tips, human lymphocytes, Chinese hamster lung, and monkey lymphocytes. Mutations were observed with oral thiotepa in mouse at doses >2.5 mg/kg (8 mg/m^2). The mouse micronucleus test was positive with IP administration of >1 mg/kg (3.2 mg/m^2). Other positive in vivo chromosomal aberration or mutation assays included Drosophila melanogaster, Chinese hamster marrow, murine marrow, monkey lymphocyte, and murine germ cell.

Impairment of Fertility

Thiotepa impaired fertility in male mice at PO or IP doses ≥0.7 mg/kg (2.24 mg/m^2), approximately 12-fold less than the maximum recommended human therapeutic dose based on body-surface area. Thiotepa (0.5 mg) inhibited implantation in female rats when instilled into the uterine cavity. Thiotepa interfered with spermatogenesis in mice at IP doses ≥0.5 mg/kg (1.6 mg/m^2), approximately 17-fold less than the maximum recommended human therapeutic dose based on body-surface area. Thiotepa interfered with spermatogenesis in hamsters at an IP dose of 1 mg/kg (4.1 mg/m^2), approximately 7-fold less than the maximum recommended human therapeutic dose based on body-surface area.

Pregnancy: Teratogenic Effects - Category D

See WARNINGS section.

Thiotepa can cause fetal harm when administered to a pregnant woman. Thiotepa given by the IP route was teratogenic in mice at doses ≥1 mg/kg (3.2 mg/m^2), approximately 8-fold less than the maximum recommended human therapeutic dose based on body-surface area. Thiotepa given by the IP route was teratogenic in rats at doses ≥3 mg/kg (21 mg/m^2), approximately equal to the maximum recommended human therapeutic dose based on body-surface area. Thiotepa was lethal to rabbit fetuses at a dose of 3 mg/kg (41 mg/ m^2), approximately 2 times the maximum recommended human therapeutic dose based on body-surface area. Patients of childbearing potential should be advised to avoid pregnancy. There are no adequate and well-controlled studies in pregnant women. If thiotepa is used during pregnancy, or if pregnancy occurs during thiotepa therapy, the patient and partner should be apprised of the potential hazard to the fetus.

Nursing Mothers

It is not known whether thiotepa is excreted in human milk. Because many drugs are excreted in human milk and because of the potential for tumorigenicity shown for thiotepa in animal studies, a decision should be made whether to discontinue nursing or to discontinue the drug, taking into account the importance of the drug to the mother.

Pediatric Use

Safety and effectiveness in pediatric patients have not been established.

Geriatric Use

Clinical studies of thiotepa did not include sufficient numbers of subjects aged 65 and over to determine whether elderly subjects respond differently from younger subjects, and other reported clinical experience has not identified differences in responses between the elderly and younger patients. In general, dose selection for an elderly patient should be cautious, usually starting at the low end of the dosing range, reflecting the greater frequency of decreasing hepatic, renal or cardiac function, and of concomitant disease or other drug therapy.

ADVERSE REACTIONS

In addition to its effect on the blood-forming elements (see WARNINGS and PRECAUTIONS sections), thiotepa may cause other adverse reactions.

General: Fatigue, weakness. Febrile reaction and discharge from a subcutaneous lesion may occur as the result of breakdown of tumor tissue.

Hypersensitivity Reactions: Allergic reactions - rash, urticaria, laryngeal edema, asthma, anaphylactic shock, wheezing.

Local Reactions: Contact dermatitis, pain at the injection site.

Gastrointestinal: Nausea, vomiting, abdominal pain, anorexia.

Renal: Dysuria, urinary retention. There have been rare reports of chemical cystitis or hemorrhagic cystitis following intravesical, but not parenteral administration of thiotepa.

Respiratory: Prolonged apnea has been reported when succinylcholine was administered prior to surgery, following combined use of thiotepa and other anticancer agents. It was theorized that this was caused by decrease of pseudocholinesterase activity caused by the anticancer drugs.

Neurologic: Dizziness, headache, blurred vision.

Skin: Dermatitis, alopecia. Skin depigmentation has been reported following topical use.

Special Senses: Conjunctivitis.

Reproductive: Amenorrhea, interference with spermatogenesis.

OVERDOSAGE

Hematopoietic toxicity can occur following overdose, manifested by a decrease in the white cell count and/or platelets. Red blood cell count is a less accurate indicator of thiotepa toxicity. Bleeding manifestations may develop. The patient may become more vulnerable to infection, and less able to combat such infection.

Dosages within and minimally above the recommended therapeutic doses have been associated with potentially life-threatening hematopoietic toxicity. Thiotepa has a toxic effect on the hematopoietic system that is dose related.

Thiotepa is dialyzable.

There is no known antidote for overdosage with thiotepa. Transfusions of whole blood or platelets have proven beneficial to the patient in combating hematopoietic toxicity.

DOSAGE AND ADMINISTRATION

Since absorption from the gastrointestinal tract is variable, thiotepa for injection should not be administered orally.

Dosage must be carefully individualized. A slow response to thiotepa for injection does not necessarily indicate a lack of effect. Therefore, increasing the frequency of dosing may only increase toxicity. After maximum benefit is obtained by initial therapy, it is necessary to continue the patient on maintenance therapy (1 to 4 week intervals). In order to continue optimal effect, maintenance doses should not be administered more frequently than weekly in order to preserve correlation between dose and blood counts.

Preparation and Administration Precautions

Thiotepa for injection is a cytotoxic anticancer drug and as with other potentially toxic compounds, caution should be exercised in handling and preparation of thiotepa for injection. Skin reactions associated with accidental exposure to thiotepa for injection may occur. The use of gloves is recommended. If thiotepa solution contacts the skin, immediately wash the skin thoroughly with soap and water. If thiotepa for injection contacts mucous membranes, the membranes should be flushed thoroughly with water.

Preparation of Solution

Thiotepa for injection should be reconstituted with 1.5 mL of sterile water for injection resulting in a drug concentration of approximately 10 mg per mL. The actual withdrawable quantities and concentration achieved are illustrated in the following table:

Label Claim (mg per vial) | Actual Content (mg per vial) | Amount of Diluent to be Added (mL) | Approximate Withdrawable Volume (mL) | Approximate Withdrawable Amount (mg per vial) | Approximate Reconstituted Concentration (mg per mL)
15 | 15.6 | 1.5 | 1.4 | 14.7 | 10.4

The reconstituted solution is hypotonic and should be further diluted with sodium chloride injection (0. 9% sodium chloride) before use.

When reconstituted with sterile water for injection, solutions of thiotepa should be stored in a refrigerator and used within 8 hours. Reconstituted solutions further diluted with sodium chloride injection should be used immediately.

Parenteral drug products should be inspected visually for particulate matter and discoloration prior to administration, whenever solution and container permit.

In order to eliminate haze, filter solutions through a 0.22 micron filter* prior to administration. Filtering does not alter solution potency. Reconstituted solutions should be clear. Solutions that remain opaque or precipitate after filtration should not be used.

*Polysulfone membrane (Gelman's Sterile Aerodisc®, Single Use) or triton-free mixed ester of cellulose/PVC (Millipore's MILLEX®-GS Filter Unit).

Initial and Maintenance Doses

Initially the higher dose in the given range is commonly administered. The maintenance dose should be adjusted weekly on the basis of pretreatment control blood counts and subsequent blood counts.

Intravenous Administration

Thiotepa for injection may be given by rapid intravenous administration in doses of 0.3 to 0.4 mg/kg. Doses should be given at 1 to 4 week intervals.

Intracavitary Administration

The dosage recommended is 0.6 to 0.8 mg/kg. Administration is usually effected through the same tubing which is used to remove the fluid from the cavity involved.

Intravesical Administration

Patients with papillary carcinoma of the bladder are dehydrated for 8 to 12 hours prior to treatment. Then 60 mg of thiotepa for injection in 30 to 60 mL of Sodium Chloride Injection is instilled into the bladder by catheter. For maximum effect, the solution should be retained for 2 hours. If the patient finds it impossible to retain 60 mL for 2 hours, the dose may be given in a volume of 30 mL. If desired, the patient may be positioned every 15 minutes for maximum area contact. The usual course of treatment is once a week for 4 weeks. The course may be repeated if necessary, but second and third courses must be given with caution since bone-marrow depression may be increased. Deaths have occurred after intravesical administration, caused by bone-marrow depression from systemically absorbed drug.

Handling and Disposal

Follow safe cytotoxic agent handling procedures. Several guidelines on this subject have been published.^1-7 There is no general agreement that all of the procedures recommended in the guidelines are necessary or appropriate.

HOW SUPPLIED

Thiotepa for Injection, USP is supplied as follows:

NDC | Thiotepa for Injection, USP | Package Factor
25021-246-02 | 15 mg Single-Dose Vial | 1 vial per carton

Storage Conditions

Store refrigerated between 2° to 8°C (36° to 46°F).

Protect from light.

Discard unused portion.

Lyophilized

Sterile, Nonpyrogenic, Preservative-free.
The container closure is not made with natural rubber latex.

For Product Inquiry call 1-866-625-1618.

REFERENCES

1. Recommendations for the Safe Handling of Parenteral Antineoplastic Drugs. NIH Publication No. 83-2621. For sale by the Superintendent of Documents, US Government Printing Office, Washington, DC 20402.
2. AMA Council Report. Guidelines for Handling Parenteral Antineoplastics. JAMA. 1985; 253(11):1590-1592.
3. National Study Commission on Cytotoxic Exposure - Recommendations for Handling Cytotoxic Agents. Available from Louis P. Jeffrey, ScD, Chairman, National Study Commission on Cytotoxic Exposure, Massachusetts College of Pharmacy and Allied Health Sciences, 179 Longwood Avenue, Boston, Massachusetts 02115.
4. Clinical Oncological Society of Australia: Guidelines and recommendations for safe handling of antineoplastic agents. Med J Australia. 1983; 1:426-428.
5. Jones RB, et al. Safe handling of chemotherapeutic agents: A report from the Mount Sinai Medical Center. Ca - A Cancer Journal for Clinicians. Sept/Oct 1983; 258-263.
6. American Society of Hospital Pharmacists technical assistance bulletin on handling cytotoxic and hazardous drugs. Am J Hosp Pharm. 1990; 47:1033-1049.
7. Controlling Occupational Exposure to Hazardous Drugs. (OSHA WORK-PRACTICE GUIDELINES). AM J Health-Syst Pharm. 1996:53:1669-1685.

Brands listed are the trademarks of their respective owners.

sagent®
Mfd. for SAGENT Pharmaceuticals
Schaumburg, IL 60173 (USA)
Made in China
©2025 Sagent Pharmaceuticals
Revised: May 2025

PACKAGE LABEL – PRINCIPAL DISPLAY PANEL – Vial Label

NDC 25021-246-02

Rx only

Thiotepa for Injection, USP

15 mg per vial

For Intravenous, Intracavitary or Intravesical Use

Caution: Cytotoxic Agent